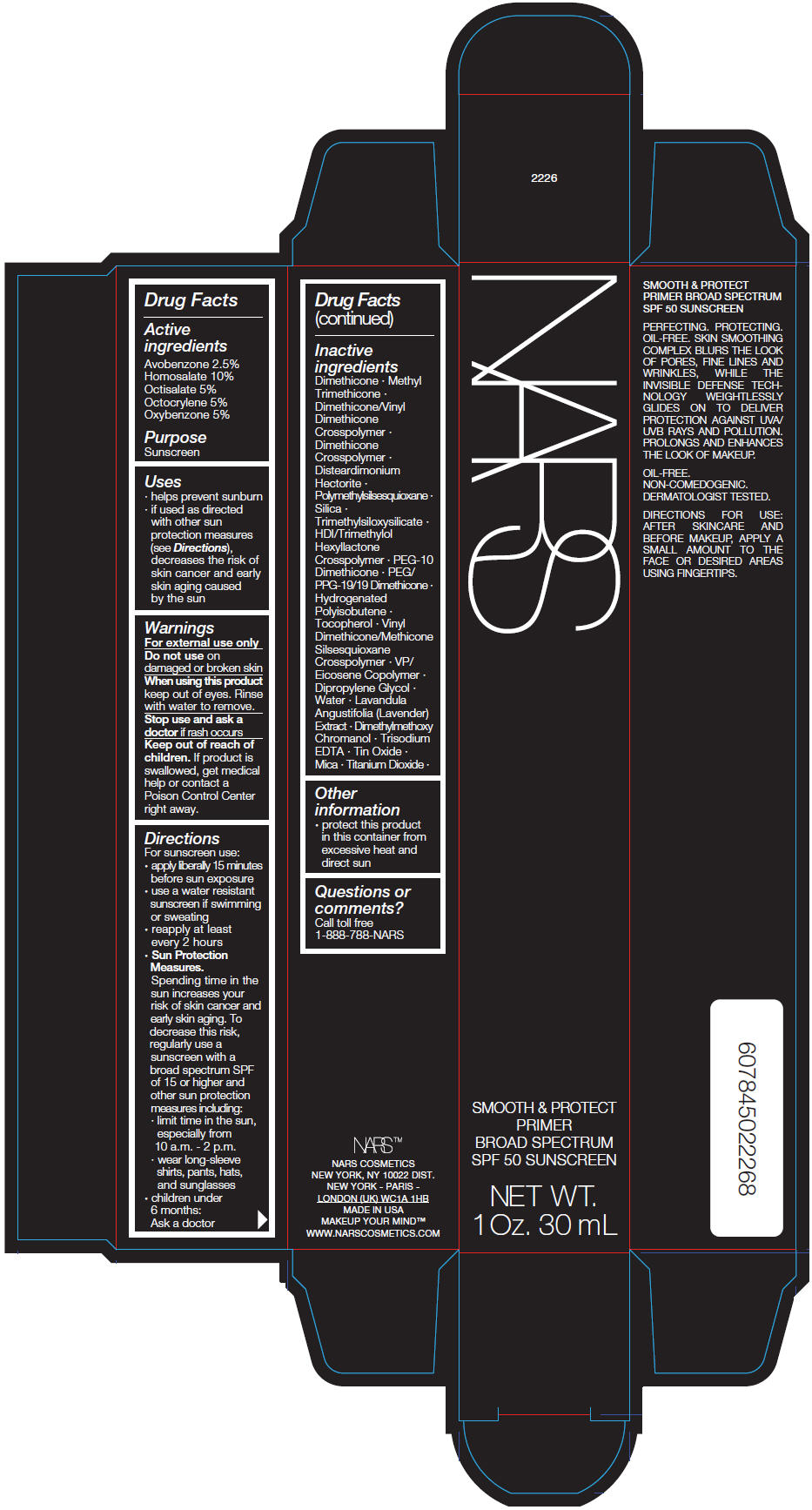 DRUG LABEL: NARS SMOOTH and PROTECT PRIMER
NDC: 13734-157 | Form: CREAM
Manufacturer: NARS Cosmetics
Category: otc | Type: HUMAN OTC DRUG LABEL
Date: 20181126

ACTIVE INGREDIENTS: AVOBENZONE 741.7 mg/30 mL; HOMOSALATE 2967 mg/30 mL; OCTISALATE 1483.5 mg/30 mL; OCTOCRYLENE 1483.5 mg/30 mL; OXYBENZONE 1483.5 mg/30 mL
INACTIVE INGREDIENTS: DIMETHICONE; METHYL TRIMETHICONE; DIMETHICONE/VINYL DIMETHICONE CROSSPOLYMER (SOFT PARTICLE); DIMETHICONE CROSSPOLYMER (450000 MPA.S AT 12% IN CYCLOPENTASILOXANE); DISTEARDIMONIUM HECTORITE; POLYMETHYLSILSESQUIOXANE (4.5 MICRONS); SILICON DIOXIDE; TRIMETHYLSILOXYSILICATE (M/Q 0.6-0.8); HEXAMETHYLENE DIISOCYANATE/TRIMETHYLOL HEXYLLACTONE CROSSPOLYMER; PEG-10 DIMETHICONE (600 CST); PEG/PPG-19/19 DIMETHICONE; HYDROGENATED POLYISOBUTENE (1300 MW); .ALPHA.-TOCOPHEROL; VINYL DIMETHICONE/METHICONE SILSESQUIOXANE CROSSPOLYMER; VINYLPYRROLIDONE/EICOSENE COPOLYMER; DIPROPYLENE GLYCOL; WATER; LAVANDULA ANGUSTIFOLIA SUBSP. ANGUSTIFOLIA FLOWERING TOP; DIMETHYLMETHOXY CHROMANOL; TITANIUM DIOXIDE; MICA; EDETATE TRISODIUM; STANNIC OXIDE

NARS SMOOTH & PROTECT PRIMER

Drug Facts

Active ingredients

Avobenzone 2.5%
Homosalate 10%
Octisalate 5%
Octocrylene 5%
Oxybenzone 5%

Purpose

Sunscreen

Uses

- helps prevent sunburn
- if used as directed with other sun protection measures (see Directions), decreases the risk of skin cancer and early skin aging caused by the sun

Warnings

For external use only

Do not use on damaged or broken skin

When using this product keep out of eyes. Rinse with water to remove.

Stop use and ask a doctor if rash occurs

Keep out of reach of children. If product is swallowed, get medical help or contact a Poison Control Center right away.

Directions

For sunscreen use:

- apply liberally 15 minutes before sun exposure
- use a water resistant sunscreen if swimming or sweating
- reapply at least every 2 hours
- Sun Protection Measures.
  Spending time in the sun increases your risk of skin cancer and early skin aging. To decrease this risk, regularly use a sunscreen with a broad spectrum SPF of 15 or higher and other sun protection measures including:
  - limit time in the sun, especially from 10 a.m. - 2 p.m.
  - wear long-sleeve shirts, pants, hats, and sunglasses
- children under 6 months: Ask a doctor

Inactive ingredients

Dimethicone ∙ Methyl Trimethicone ∙ Dimethicone/Vinyl Dimethicone Crosspolymer ∙ Dimethicone Crosspolymer ∙ Disteardimonium Hectorite ∙ Polymethylsilsesquioxane ∙ Silica ∙ Trimethylsiloxysilicate ∙ HDI/Trimethylol Hexyllactone Crosspolymer ∙ PEG-10 Dimethicone ∙ PEG/PPG-19/19 Dimethicone ∙ Hydrogenated Polyisobutene ∙ Tocopherol ∙ Vinyl Dimethicone/Methicone Silsesquioxane Crosspolymer ∙ VP/Eicosene Copolymer ∙ Dipropylene Glycol ∙ Water ∙ Lavandula Angustifolia (Lavender) Extract ∙ Dimethylmethoxy Chromanol ∙ Trisodium EDTA ∙ Tin Oxide ∙ Mica ∙ Titanium Dioxide ∙

Other information

- protect this product in this container from excessive heat and direct sun

Questions or comments?

Call toll free 1-888-788-NARS

PRINCIPAL DISPLAY PANEL - 30 mL Tube Carton

NARS

SMOOTH & PROTECT
PRIMER
BROAD SPECTRUM
SPF 50 SUNSCREEN

NET WT.
1 Oz. 30 mL